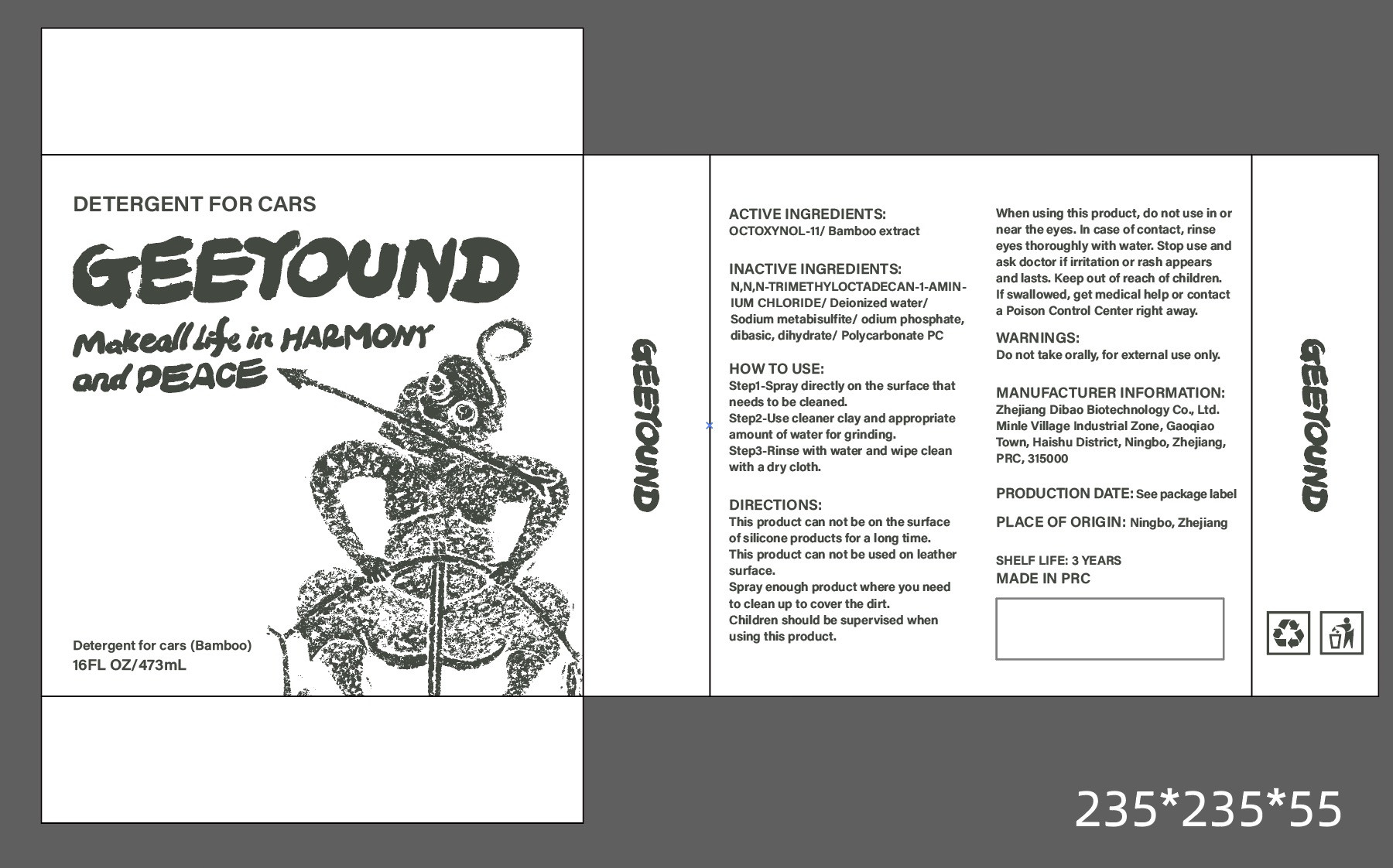 DRUG LABEL: Detergent for cars
NDC: 82371-002 | Form: LIQUID
Manufacturer: Zhejiang Dibao Biotechnology Co., Ltd.
Category: otc | Type: HUMAN OTC DRUG LABEL
Date: 20211230

ACTIVE INGREDIENTS: OCTOXYNOL-11 4 g/100 mL; BAMBUSA VULGARIS TOP 3.2 g/100 mL
INACTIVE INGREDIENTS: SODIUM METABISULFITE; SODIUM PHOSPHATE, DIBASIC, DIHYDRATE; TRIMETHYL OCTADECYL AMMONIUM CHLORIDE; WATER

ACTIVE INGREDIENT

OCTOXYNOL-11 4%

Bamboo extract 3.2%

INACTIVE INGREDIENT

Deionized water

Sodium metabisulfite

Sodium phosphate, dibasic, dihydrate

Polycarbonate PC

N,N,N-TRIMETHYLOCTADECAN-1-AMINIUM CHLORIDE

HOW TO USE

Step1-Spray directly on the surface thatneeds to be cleaned.
Step2-Use cleaner clay and appropriate amount of water for grinding.
Step3-Rinse with water and wipe cleanwith a dry cloth.

DIRECTIONS

This product can not be on the surface of silicone products for a long time.This product can not be used on leather surface.
Spray enough product where you need to clean up to cover the dirt.
Children should be supervised when using this product.
When using this product, do not use in or near the eyes. In case of contact, rinse eyes thoroughly with water. Stop use and ask doctor if irritation or rash appears and lasts. Keep out of reach of children.If swallowed, get medical help or contact a Poison Control Center right away.

Keep out of reach of children

PURPOSE

clean

STORAGE AND HANDLING

Keep in a cool and dry place

WARNINGS

Do not take orally, for external use only.